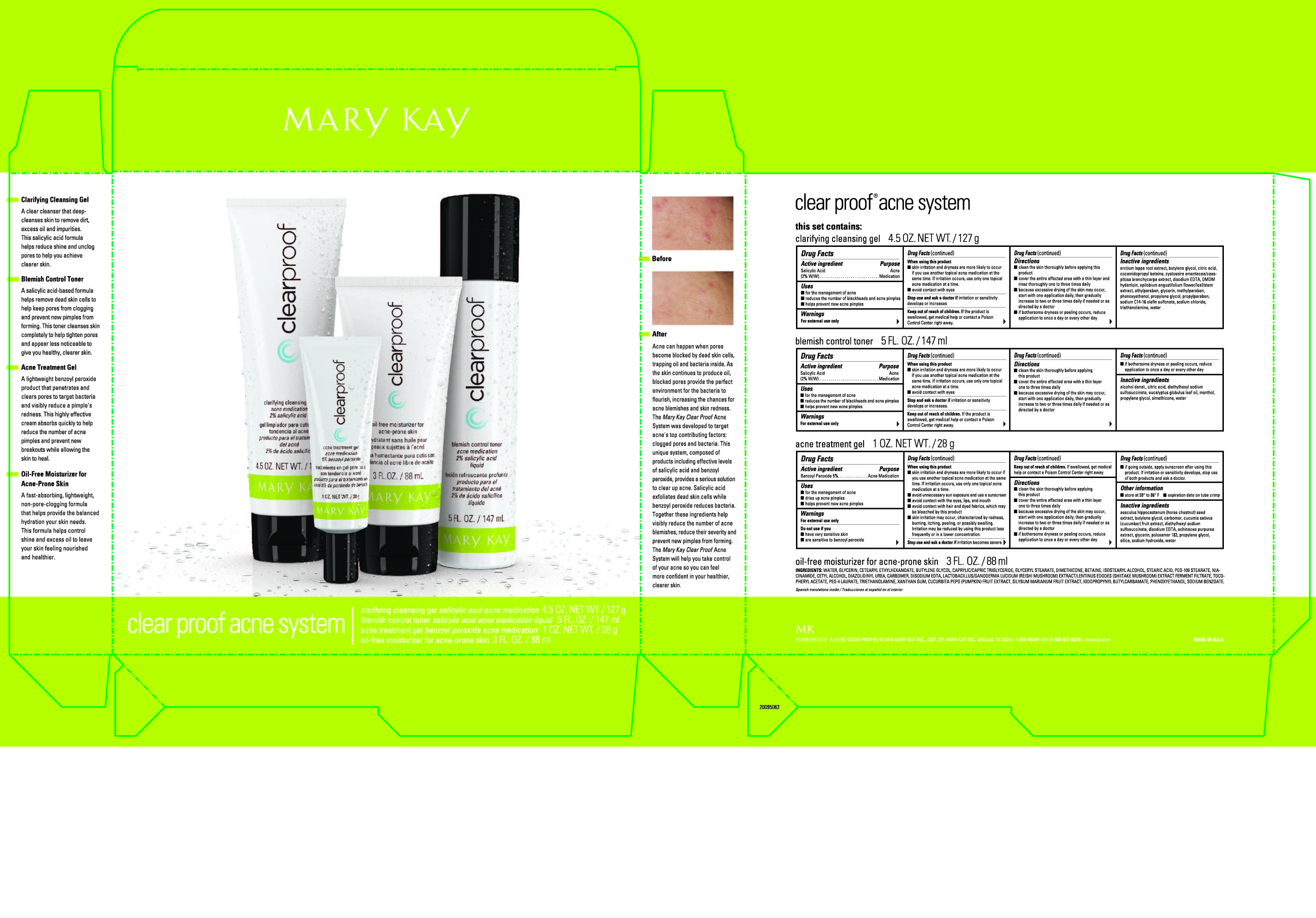 DRUG LABEL: Clear Proof Acne System
NDC: 51531-8977 | Form: KIT | Route: TOPICAL
Manufacturer: Mary Kay Inc.
Category: otc | Type: HUMAN OTC DRUG LABEL
Date: 20241217

ACTIVE INGREDIENTS: BENZOYL PEROXIDE 5 g/100 g; SALICYLIC ACID 2 g/100 mL; SALICYLIC ACID 2 g/100 g
INACTIVE INGREDIENTS: WATER; PROPYLENE GLYCOL; POLOXAMER 182; SILICON DIOXIDE; CARBOMER INTERPOLYMER TYPE A (ALLYL SUCROSE CROSSLINKED); SODIUM HYDROXIDE; DOCUSATE SODIUM; EDETATE DISODIUM; GLYCERIN; BUTYLENE GLYCOL; ECHINACEA PURPUREA; CUCUMBER; HORSE CHESTNUT; WATER; ALCOHOL; DENATONIUM BENZOATE; TERT-BUTYL ALCOHOL; PROPYLENE GLYCOL; CITRIC ACID MONOHYDRATE; DOCUSATE SODIUM; EUCALYPTUS OIL; MENTHOL; DIMETHICONE; SILICON DIOXIDE; BUTYLENE GLYCOL; CITRIC ACID MONOHYDRATE; PROPYLENE GLYCOL; METHYLPARABEN; ETHYLPARABEN; DMDM HYDANTOIN; ARCTIUM LAPPA ROOT; PROPYLPARABEN; GLYCERIN; EPILOBIUM ANGUSTIFOLIUM FLOWERING TOP; SODIUM C14-16 OLEFIN SULFONATE; WATER; COCAMIDOPROPYL BETAINE; SODIUM CHLORIDE; TROLAMINE; EDETATE DISODIUM; PHENOXYETHANOL

Mary Kay
Clear Proof Acne System

Clarifying Cleansing Gel

Drug Facts

Active ingredient

Salicylic Acid (2% W/W)

Purpose

Acne Medication

Uses

- for the management of acne
- reduces the number of blackheads and acne pimples
- helps prevent new acne pimples

Warnings

For external use only

When using this product

- skin irritation and dryness is more likely to occur if you use another topical acne medication at the same time. If irritation occurs, only use one topical acne medication at a time.
- avoid contact with the eyes

Stop use and ask a doctor if

irritation or sensitivity develops or occurs

Keep our of reach of children.

If swallowed, get medical help or contact a Poison Control Center right away.

Directions

- cleanse skin thoroughly before applying medication
- cover the entire affected area with a thin layer then rinse thoroughly one to three times daily
- because excessive drying of the skin may occur, start with one application daily, then gradually increase to two or three times daily if needed or as directed by a doctor
- if bothersome dryness or peeling occurs, reduce application to once a day or every other day

Inactive ingredients

arctium lappa root extract, butylene glycol, citric acid, cocamidopropyl betaine, cystoseira amentacea/caespitosa branchycarpa extract, disodium EDTA, DMDM hydantoin, epilobium angustifolium flower/leaf/stem extract, ethylparaben, glycerin, methylparben, phenoxyethanol, propylene glycol, propylparaben, sodium C14-16 olefin sulfonate, sodium chloride, triethanolamine, water

Blemish Control Toner

Drug Facts

Active ingredient

Salicylic Acid (2% W/W)

Purpose

Acne Medication

Uses

- for the management of acne
- reduces the number of blackheads and acne pimples
- helps prevent new acne pimples

Warnings

For external use only

When using this product

- skin irritation and dryness is more likely to occur if you use another topical acne medication at the same time. If irritation occurs, only use one topical acne medication at a time.
- avoid contact with the eyes

Stop use and ask a doctor if

irritation or sensitivity develops or increases

Keep out of reach of children.

If swallowed, get medical help or contact a Poison Control Center right away.

Directions

- cleanse the skin thoroughly before applying this product
- cover the entire affected area with a thin layer one to three times daily
- because excessive drying of the skin may occur, start with one application daily, then gradually increase to two or three times daily if needed or as directed by a doctor
- if bothersome dryness or peeling occurs, reduce application to once a day or every other day

Inactive ingredients

alcohol denat., citric acid, diethylhexyl sodium sulfosuccinate, eucalyptus globulus leaf oil, menthol, propylene glycol, simethicone, water

Acne Treatment Gel

Drug Facts

Active ingredient

Benzoyl Peroxide 5%

Purpose

Acne Medication

Uses

- for the management of acne
- dries up acne pimples
- helps prevent new acne pimples

Warnings

For external use only

Do not use if you

- have very sensitive skin
- are sensitive to benzoyl peroxide

When using this product

- skin irritation and dryness is more likely to occur if you use another topical acne medication at the same time. If irritation occurs, only use one topical acne medication at a time.
- avoid unnecessary sun exposure and use a sunscreen
- avoid contact with the eyes, lips, and mouth
- avoid contact with hair and dyed fabrics, which may be bleached by this product
- skin irritation may occur, characterized by redness, burning, itching, peeling, or possibly swelling. Irritation may be reduced by using the product less frequently or in a lower concentration.

Stop use and ask a doctor if

irritation becomes severe

Keep out of reach of children.

If swallowed, get medical help or contact a Poison Control Center right away.

DOSAGE AND ADMINISTRATION

- cleanse the skin thoroughly before applying this product
- cover the entire affected area with a thin layer one to three times daily
- because excessive drying of the skin may occur, start with one application daily, then gradually increase to two or three times daily if needed or as directed by a doctor
- if bothersome dryness or peeling occurs, reduce application to once a day or every other day
- if going outside, apply sunscreen after using this product. If irritation or sensitivity develops, stop use of both products and ask a doctor.

Other information

- store at 59° F to 86° F
- expiration date on tube crimp

Inactive ingredients

aesculus hippocastanum (horse chestnut) seed extract, butylene glycol, carbomer, cucumis sativus (cucumber) fruit extract, diethylhexyl sodium sulfosuccinate, disodium EDTA, echinacea purpurea extract, glycerin, poloxamer 182, propylene glycol, silica, sodium hydroxide, water

INGREDIENTS:

Water/Eau, Glycerin, Cetearyl Ethylhexanoate, Butylene Glycol, Caprylic/Capric Triglyceride, Glyceryl Stearate, Dimethicone, Isostearyl Alcohol, Stearic Acid, Betaine, Niacinamide, PEG-100 Stearate, Cetyl Alcohol, Cucurbita Pepo (Pumpkin) Fruit Extract, Silybum Marianum Fruit Extract, Tocopheryl Acetate, Lactobacillus/Ganoderma Lucidum (Reishi) Extract/Lentinus Edodes (Truncated), PEG-4 Laurate, Triethanolamine, Xanthan Gum, Carbomer, Disodium EDTA, Iodopropynyl Butylcarbamate, Phenoxyethanol, Diazolidinyl Urea, Sodium Benzoate

Principal Display Panel - kit carton

clear proof acne system

clarifying cleansing gel salicylic acid acne medication 4.5 OZ. NET WT. / 127 g

blemish control toner salicylic acid acne medication liquid 5 FL. OZ. / 147 ml

acne treatment gel benzoyl peroxide acne medication 1 OZ. NET WT. / 28 g

oil-free moisturizer for acne-prone skin 3 FL. OZ. / 88 ml